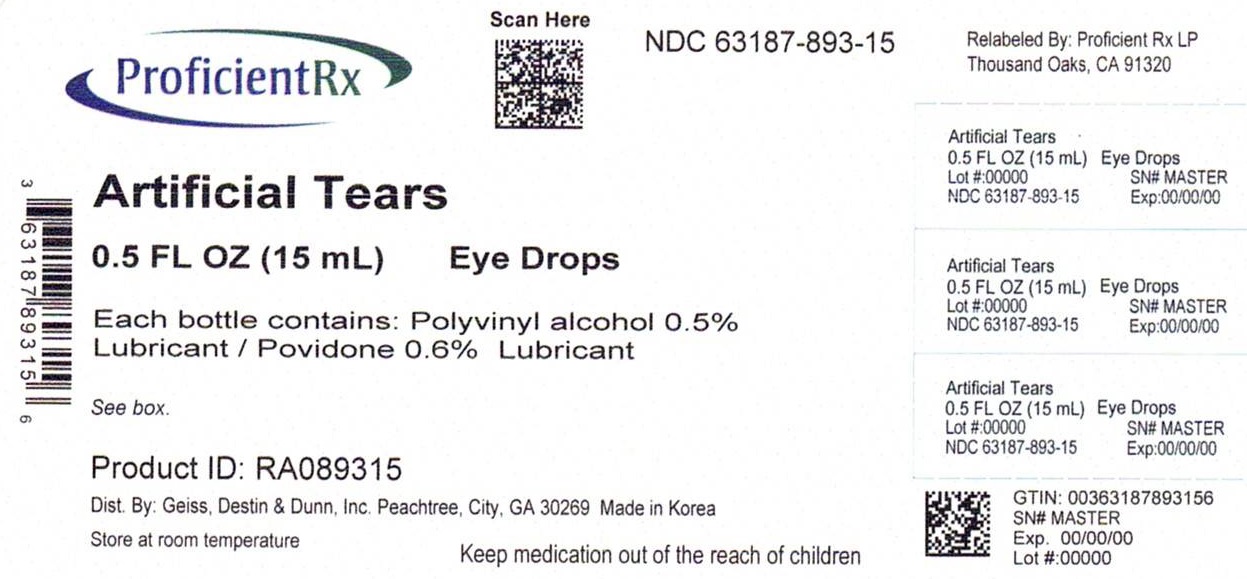 DRUG LABEL: GoodSense Artifical Tears
NDC: 63187-893 | Form: SOLUTION/ DROPS
Manufacturer: Proficient Rx LP
Category: otc | Type: HUMAN OTC DRUG LABEL
Date: 20240201

ACTIVE INGREDIENTS: POLYVINYL ALCOHOL, UNSPECIFIED 0.05 g/1 mL; POVIDONE, UNSPECIFIED 0.06 g/1 mL
INACTIVE INGREDIENTS: BENZALKONIUM CHLORIDE; SODIUM PHOSPHATE, DIBASIC, DIHYDRATE; EDETATE DISODIUM; HYDROCHLORIC ACID; SODIUM PHOSPHATE, MONOBASIC, DIHYDRATE; POTASSIUM CHLORIDE; WATER; SODIUM BICARBONATE; SODIUM CHLORIDE; SODIUM HYDROXIDE

Active ingredients Purpose

Polyvinyl alcohol 0.5%............................Lubricant

Povidone 0.6%......................................Lubricant

Uses

- For the temporary relief of burning & irritation due to dryness of the eye
- For use as a protectant against further irritation or to relieve dryness of the eye

Warnings

For external use only.

Do not use

- if solution changes color or becomes cloudy.

When using this product

- to avoid contamination, do not touch tip to any surface
- replace cap after using

Stop use and ask a doctor if

- you experience eye pain
- you experience changes in vision
- you experience continued redness or irritation of the eye
- the condition worsens
- symptoms last for more than 72 hours

Keep out of reach of children.

If swallowed, get medical help or contact a Poison Control Center right away.

Directions

- Instill 1 or 2 drops in the affected eye(s) as needed.
- store at room temperature
- remove contact lenses before using

Inactive ingredients

benzlkonium chloride, dibasic sodium phosphate hydrate, edetate disodium, glucose, hydrochloric acid, monobasic sodium phosphate, potassium chloride, purified water, sodium bicarbonate, sodium chloride, sodium citrate hydrate, sodium hydroxide

DOSAGE AND ADMINISTRATION

Distributed by:

Geiss, Destin & Dunn, Inc.

Peachtree, City, GA 30269

www.valuelabels.com

1-866-696-0957

Made in Korea

Relabeled by:

Proficient Rx LP

Thousand Oaks, CA 91320